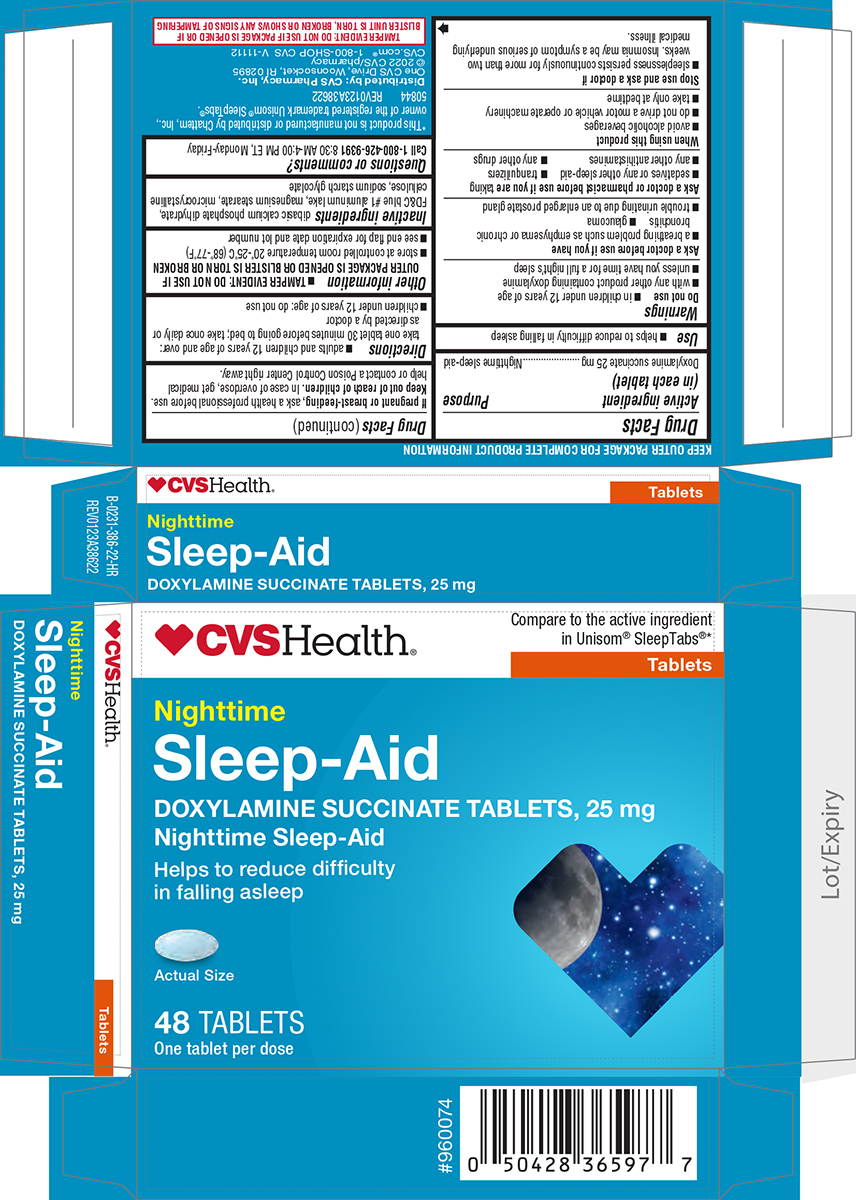 DRUG LABEL: Nighttime Sleep Aid
NDC: 69842-386 | Form: TABLET
Manufacturer: CVS PHARMACY
Category: otc | Type: HUMAN OTC DRUG LABEL
Date: 20250819

ACTIVE INGREDIENTS: DOXYLAMINE SUCCINATE 25 mg/1 1
INACTIVE INGREDIENTS: DIBASIC CALCIUM PHOSPHATE DIHYDRATE; FD&C BLUE NO. 1 ALUMINUM LAKE; MAGNESIUM STEARATE; MICROCRYSTALLINE CELLULOSE; SODIUM STARCH GLYCOLATE TYPE A POTATO

CVS 44-386 Delisted

Active ingredient (in each tablet)

Doxylamine succinate 25 mg

Purpose

Nighttime sleep-aid

Use

- helps to reduce difficulty in falling asleep

Warnings

Do not use

- in children under 12 years of age
- with any other product containing doxylamine
- unless you have time for a full night’s sleep

Ask a doctor before use if you have

- a breathing problem such as asthma, emphysema or chronic bronchitis
- difficulty in urination due to enlargement of the prostate gland
- glaucoma

Ask a doctor or pharmacist before use if you are

taking

- sedatives or any other sleep-aid
- tranquilizers
- any other antihistamines
- any other drugs

When using this product

- avoid alcoholic beverages
- do not drive a motor vehicle or operate machinery
- take only at bedtime

Stop use and ask a doctor if

- sleeplessness persists continuously for more than two weeks. Insomnia may be a symptom of serious underlying medical illness.

If pregnant or breast-feeding,

ask a health professional before use.

Keep out of reach of children.

In case of overdose, get medical help or contact a Poison Control Center right away.

Directions

- adults and children 12 years of age and over: take one tablet 30 minutes before going to bed; take once daily or as directed by a doctor
- children under 12 years of age: do not use

Other information

- TAMPER EVIDENT: DO NOT USE IF OUTER PACKAGE IS OPENED OR BLISTER IS TORN OR BROKEN
- store at controlled room temperature 20°-25°C (68°-77°F)
- see end flap for expiration date and lot number

Inactive ingredients

dibasic calcium phosphate dihydrate, FD&C blue #1 aluminum lake, magnesium stearate, microcrystalline cellulose, sodium starch glycolate

Questions or comments?

Call 1-800-426-9391 8:30 AM-4:00 PM ET, Monday-Friday

Principal Display Panel

♥︎CVSHealth®

Compare to the active ingredient
in Unisom® SleepTabs®*

Tablets

Nighttime
Sleep-Aid
DOXYLAMINE SUCCINATE TABLETS, 25 mg
Nighttime Sleep-Aid

Helps to reduce difficulty
in falling asleep

Actual Size

48 TABLETS
One tablet per dose

TAMPER EVIDENT: DO NOT USE IF PACKAGE IS OPENED OR IF
BLISTER UNIT IS TORN, BROKEN OR SHOWS ANY SIGNS OF TAMPERING

*This product is not manufactured or distributed by Chattem, Inc.,
owner of the registered trademark Unisom® SleepTabs®.
50844 REV0123A38622

Distributed by: CVS Pharmacy, Inc.
One CVS Drive, Woonsocket, RI 02895
© 2022 CVS/pharmacy
CVS.com® 1-800-SHOP CVS V-11112

CVS 44-386